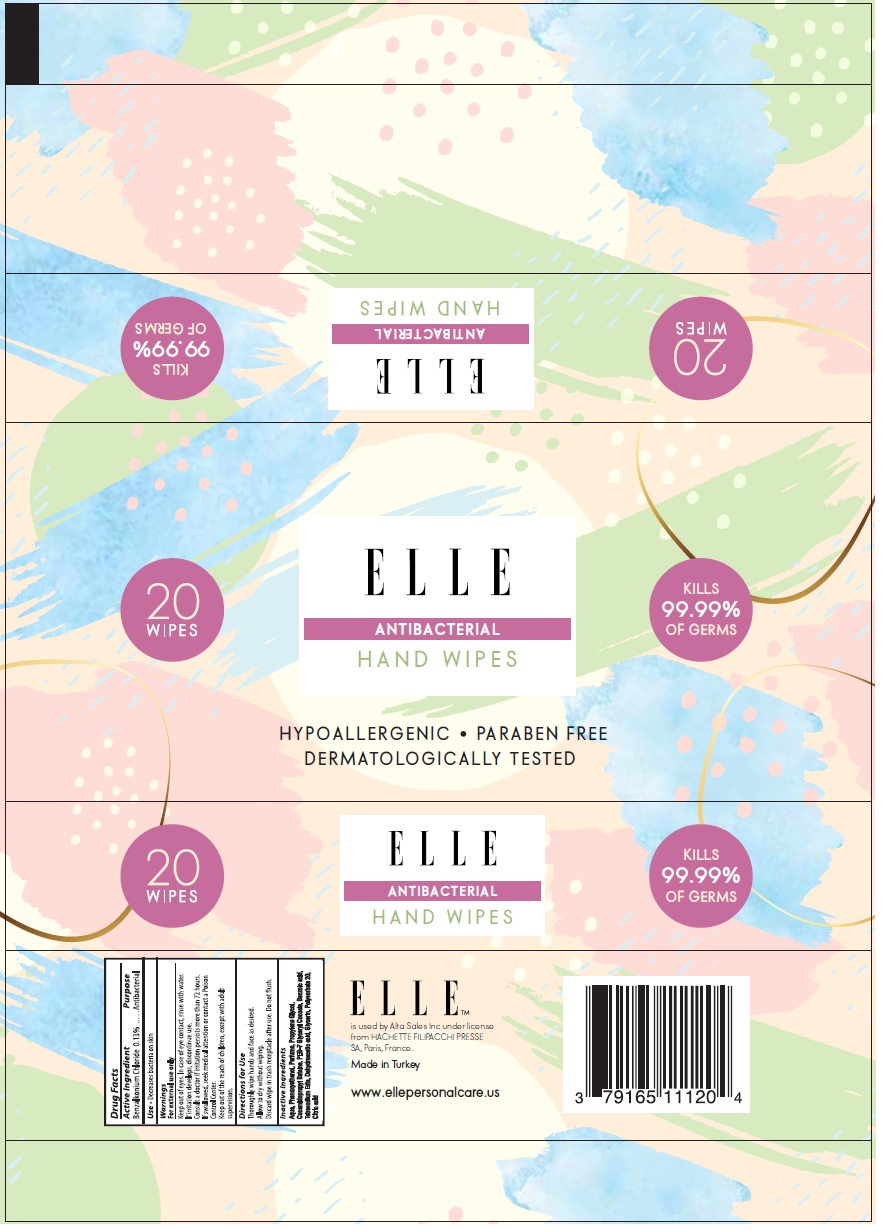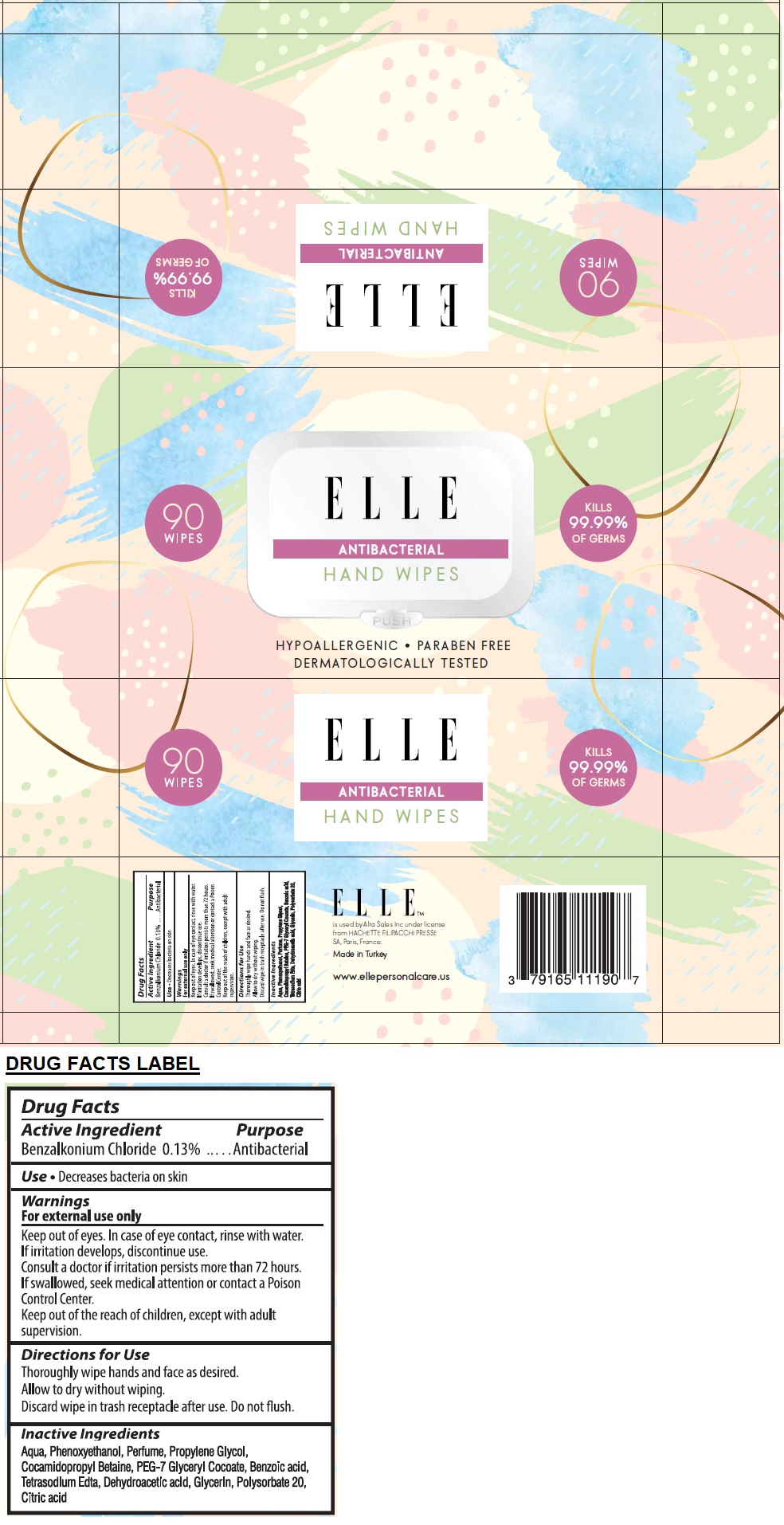 DRUG LABEL: ELLE ANTIBACTERIAL HAND WIPES
NDC: 79165-111 | Form: CLOTH
Manufacturer: Alta Sales Inc
Category: otc | Type: HUMAN OTC DRUG LABEL
Date: 20200827

ACTIVE INGREDIENTS: BENZALKONIUM CHLORIDE 0.13 g/100 g
INACTIVE INGREDIENTS: WATER; PHENOXYETHANOL; PROPYLENE GLYCOL; COCAMIDOPROPYL BETAINE; PEG-7 GLYCERYL COCOATE; BENZOIC ACID; EDETATE SODIUM; DEHYDROACETIC ACID; GLYCERIN; POLYSORBATE 20; CITRIC ACID MONOHYDRATE

ELLE ANTIBACTERIAL HAND WIPES

Active Ingredient

Benzalkonium Chloride 0.13%

Purpose

Antibacterial

INDICATIONS AND USAGE

Use • Decreases bacteria on skin

Warnings

For external use only

Keep out of eyes. In case of eye contact, rinse with water.

If irritation develops, discontinue use.

Consult a doctor if irritation persists more than 72 hours.

If swallowed, seek medical attention or contact a Poison Control Center.

KEEP OUT OF REACH OF CHILDREN

Keep out of the children, except with adult supervision.

Directions for use

Thoroughly wipe hands and face as desired.

Allow to dry without wiping.

Discard wipe in trash receptacle after use. Do not flush.

Inactive ingredients

Aqua, Phenoxyethanol, Perfume, Propylene Glycol, Cocamidopropyl Betaine, PEG-7 Glyceryl Cocoate, Benzoic acid, Tetrasodium Edta, Dehydroacetic acid, Glycerin, Polysorbate 20, Citric acid

KILLS 99.99% OF GERMS

HYPOALLERGENIC • PARABEN FREE

DERMATOLOGICALLY TESTED

ELLE™

is used by Alta Sales Inc under license

from HACHETTE FILIPACCHI PRESSE

SA, Paris, France.

Made in Turkey

www.ellepersonalcare.us